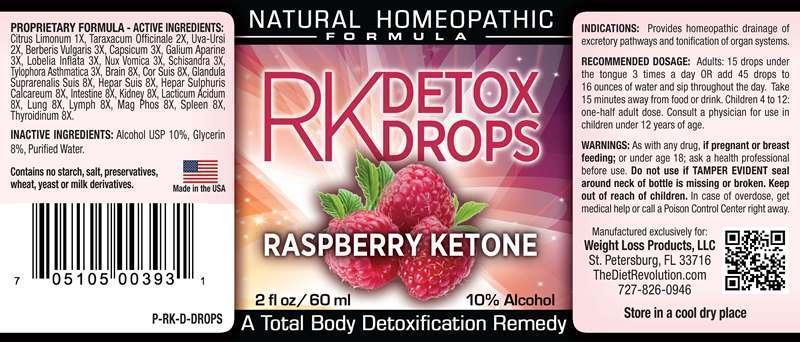 DRUG LABEL: RK Detox
NDC: 49721-0003 | Form: LIQUID
Manufacturer: Weight Loss Products, LLC
Category: homeopathic | Type: HUMAN OTC DRUG LABEL
Date: 20140825

ACTIVE INGREDIENTS: LEMON JUICE 1 [hp_X]/1 mL; TARAXACUM OFFICINALE 2 [hp_X]/1 mL; ARCTOSTAPHYLOS UVA-URSI LEAF 2 [hp_X]/1 mL; BERBERIS VULGARIS ROOT BARK 3 [hp_X]/1 mL; CAPSICUM 3 [hp_X]/1 mL; GALIUM APARINE 3 [hp_X]/1 mL; LOBELIA INFLATA 3 [hp_X]/1 mL; STRYCHNOS NUX-VOMICA SEED 3 [hp_X]/1 mL; SCHISANDRA CHINENSIS FRUIT 3 [hp_X]/1 mL; TYLOPHORA INDICA WHOLE 3 [hp_X]/1 mL; PORK BRAIN 8 [hp_X]/1 mL; SUS SCROFA ADRENAL GLAND 8 [hp_X]/1 mL; PORK HEART 8 [hp_X]/1 mL; PORK LIVER 8 [hp_X]/1 mL; CALCIUM SULFIDE 8 [hp_X]/1 mL; PORK INTESTINE 8 [hp_X]/1 mL; PORK KIDNEY 8 [hp_X]/1 mL; LACTIC ACID, DL- 8 [hp_X]/1 mL; SUS SCROFA LUNG 8 [hp_X]/1 mL; SUS SCROFA LYMPH 8 [hp_X]/1 mL; MAGNESIUM PHOSPHATE, DIBASIC TRIHYDRATE 8 [hp_X]/1 mL; SUS SCROFA SPLEEN 8 [hp_X]/1 mL; SUS SCROFA THYROID 8 [hp_X]/1 mL
INACTIVE INGREDIENTS: WATER; GLYCERIN; ALCOHOL

DRUG FACTS:

PROPRIETARY FORMULA - ACTIVE INGREDIENTS:

Citrus Limonum 1X, Taraxacum Officinale 2X, Uva Ursi 2X, Berberis Vulgaris 3X, Capsicum Annuum 3X, Galium Aparine 3X, Lobelia Inflata 3X, Nux Vomica 3X, Schisandra 3X, Tylophora Asthmatica 3X, Brain (suis) 8X, Glandula Suprarenalis Suis 8X, Heart (suis) 8X, Hepar Suis 8X, Hepar sulphuris Calcareum 8X, Intestine (suis) 8X, Kidney (suis) 8X, Lacticum Acidum 8X, Lung (suis) 8X, Lymph (suis) 8X, Magnesia Phosphorica 8X, Spleen (suis) 8X, Throidinum (suis) 8X,

INDICATIONS:

Provides homeopathic drainage of excretory pathways and tonification of organ systems.

WARNINGS:

As with any drug, if pregnant or breast feeding; or under age 18; ask a health professional before use. Do not use if TAMPER EVIDENT seal around neck of bottle is missing or broken. Keep out of reach of children. In case of overdose, get medical help or call a Poison Control Center right away.

Store in a cool dry place

Keep out of reach of children. In case of overdose, get medical help or call a Poison Control Center right away.

Recommended Dosage:

Adults: 15 drops under the tongue 3 times a day OR add 45 drops to 16 ounces of water and sip throughout the day. Take 15 minutes away from food or drink. Children 4 to 12: one-half adult dose. Consult a physician for use in children under 12 years of age.

INDICATIONS:

Provides homeopathic drainage of excretory pathways and tonification of organ systems.

INACTIVE INGREDIENTS:

Alcohol USP 10%, Glycerin 8%, Purified Water.

Contains no starch, salt, preservatives, wheat, yeast or mild derivatives.

QUESTIONS:

Manufactured exclusively for:

Weight Loss Products, LLC

St. Petersburg, FL 33716

TheDietRevalution.com

727-826-0946

PACKAGE LABEL DISPLAY

NATURAL HOMEOPATHIC

FORMULA

RK DETOX DROPS

RASPBERRY KETONE

2 fl oz/60 ml

A Total Body Detoxification Remedy